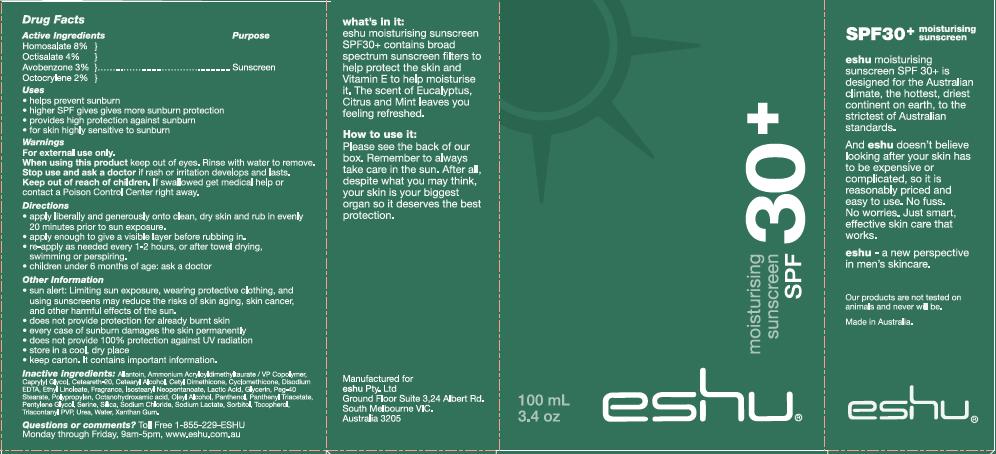 DRUG LABEL: Eshu Skin Assist SPF 30 
NDC: 42315-002 | Form: LOTION
Manufacturer: Eshu Pty. Ltd.
Category: otc | Type: HUMAN OTC DRUG LABEL
Date: 20110217

ACTIVE INGREDIENTS: HOMOSALATE 8 mL/100 mL; OCTISALATE 4 mL/100 mL; AVOBENZONE 3 mL/100 mL; OCTOCRYLENE 2 mL/100 mL
INACTIVE INGREDIENTS: ALLANTOIN; CAPRYLYL GLYCOL; CETOSTEARYL ALCOHOL; ETHYL LINOLEATE; LACTIC ACID; GLYCERIN; PEG-40 STEARATE; PANTHENOL; PENTYLENE GLYCOL; SERINE; SILICON DIOXIDE; SODIUM CHLORIDE; SODIUM LACTATE; SORBITOL; UREA; WATER

ACTIVE INGREDIENT

Homosalate 8%

Octisalate 4%

Avobenzone 3%

Octocrylene 2%

PURPOSE

Sunscreen

INDICATIONS AND USAGE

- helps prevent sunburn
- higher SPF gives more sunburn protection
- provides high protection against sunburn
- for skin highly sensitive to sunburn

WARNINGS

For external use only.

When using this product, keep out of eyes. Rinse with water to remove.

Stop use and ask a doctor if rash or irritation develops and lasts.

Keep out of reach of children. If swallowed get medical help or contact a Poison Control Center right away.

DOSAGE AND ADMINISTRATION

- apply liberally and generously onto clean, dry skin and rub in evenly 20 minutes prior to sun exposure
- apply enough to give a visible layer before rubbing in
- re-apply as needed every 1-2 hours, or after towel drying, swimming, or perspiring
- children under 6 months of age: ask a doctor

STORAGE AND HANDLING

- sun alert: Limiting sun exposure, wearing protective clothing, and using sunscreens may reduce the risks of skin aging, skin cancer and other harmful effects of the sun
- does not provide protection for already burnt skin
- every case of sunburn damages the skin permanently
- does not provide 100% protection against UV radiation
- store in a cool, dry place
- keep carton. It contains important information

INACTIVE INGREDIENT

Allantoin, Ammonium Acryloydimethyltaurate/VP Copolymer, Caprylyl Glycol, Ceteareth-20, Cetearyl Alcohol, Cetyl Dimethicone, Cyclomethicone, Disodium EDTA, Ethyl Linoleate, Fragrance, Isostearyl Neopentanoate, Lactic Acid, Glycerin, PEG-40 Stearate, Polypropylene, Xantham Gum, Octanohydroxamic acid, Oleyl Alcohol, Panthenol, Panthenyl Triacetate, Pentylene Glycol, Serine, Silica, Sodium Chloride, Sodium Lactate, Sorbitol, Tocopherol, Triacontanyl PVP, Urea, Water

Questions or Comments? Toll Free 1-855-229-ESHU

Monday through Friday, 9am-5pm, www.eshu.com.au

PACKAGE LABEL

What's in it:

eshu moisturising sunscreen SPF30+ contains broad spectrum sunscreen filters to help protect the skin and Vitamin E to help moisturise it. The scent of Eucalyptus, Citrus and Mint leaves you feeling refreshed.

How to use it:

Please see the back of our box. Remember to always take care in the sun. After all, despite what you may think, your skin is your biggest organ so it deserves the best protection.

eshu moisturising sunscreen SPF30+ is designed for the Australian climate, the hottest, driest continent on earth, to the strictest of Australian standards.

And eshu doesn't believe looking after your skin has to be expensive or complicated, so it is reasonably priced and easy to use. No fuss. No worries. Just smart, effective skin care that works.

eshu - a new perspective in men's skincare.\